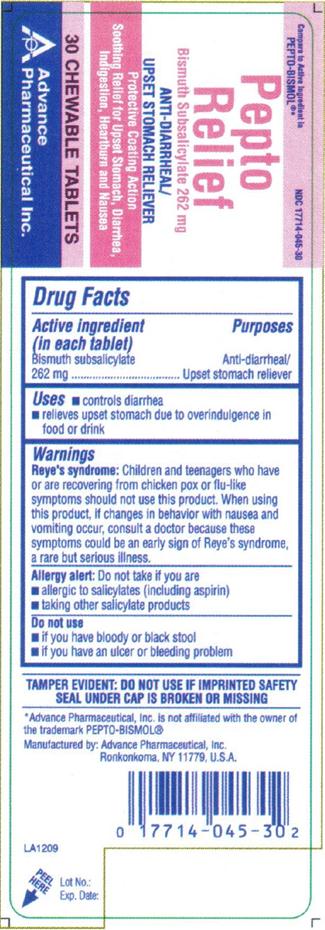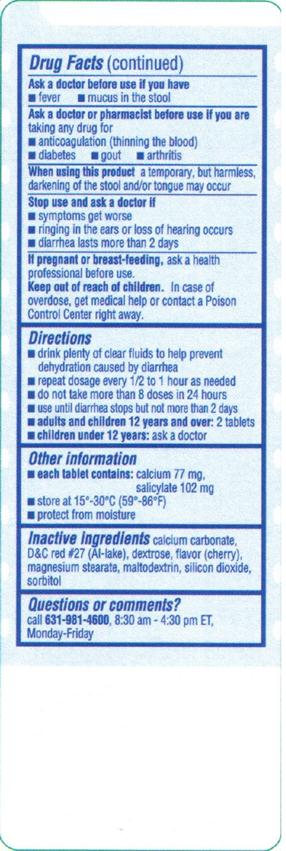 DRUG LABEL: Pepto Relief
NDC: 17714-045 | Form: TABLET, CHEWABLE
Manufacturer: Advance Pharmaceutical Inc.
Category: otc | Type: HUMAN OTC DRUG LABEL
Date: 20171222

ACTIVE INGREDIENTS: BISMUTH SUBSALICYLATE 262 mg/1 1
INACTIVE INGREDIENTS: CALCIUM CARBONATE; D&C RED NO. 27; DEXTROSE; CHERRY; MAGNESIUM STEARATE; MALTODEXTRIN; SILICON DIOXIDE; SORBITOL

PEPTO RELIEF Bismuth Subsalicylate 262 MG

Drug Facts

.

Active Ingredient

(in each tablet)

Bismuth subsalicylate 262 mg

Purpose

Anti-diarrheal/Upset stomach reliever

Uses

- Controls diarrhea
- Relieves upset stomach due to overindulgence in food or drink

Warnings

Reye’s syndrome: Children and teenagers who have or are recovering from chicken pox or flu-like symptoms should not use this product. When using this product, if changes in behavior with nausea and vomiting occur, consult a doctor because these symptoms could be an early sign of Reye’s syndrome, a rare but serious illness.

Allergy alert: Do not take if you are

- allergic to salicylates (including aspirin)
- taking other salicylate products
  Do not use
- If you have bloody or black stool
- If you have an ulcer or bleeding problem
  Ask a doctor before use if you have
- Fever
- Mucus in the stool
  Ask a doctor or pharmacist before use if you are
- taking any drug for
- anticoagulation (thinning the blood)
- diabetes
- gout
- arthritis
  when using this product a temporary, but harmless, darkening of the stool and/or tongue may occur
  stop use and ask a doctor if
- symptoms get worse
- ringing in the ears or loss of hearing occurs

diarrhea lasts more than 2 days

If pregnant or breast-feeding, ask a health professional before use.

Keep out of reach of children. In case of overdose, get medical help or contact a Poison Control Center right away.

Directions

- drink plenty of clear fluids to help prevent dehydration caused by diarrhea
- repeat dosage every 1/2 to 1 hour as needed
- do not take more than 8 doses in 24 hours
- use until diarrhea stops but not more than 2 days
- adults and children 12 years and over: 2 tablets
- children under 12 years: ask a doctor

Other Information

- Each tablet contains: calcium 77 mg, salicylate 102 mg
- store at 15°-30°C (59°-86°F)
- protect from moisture

INACTIVE INGREDIENT

calcium carbonate, D&C red # 27 (Al-lake), dextrose, flavor (cherry), magnesium stearate, maltodextrin, silicon dioxide, sorbitol

Questions or Comments

TAMPER EVIDENT: DO NOT USE IF IMPRINTED SAFETY SEAL UNDER CAP IS BROKEN OR MISSING

Call 631-981-4600, 8.30 am – 4.30 pm EST Monday - Friday

Package Label

NDC: 17714-045-30 – 30 CHEWABLE TABLETS